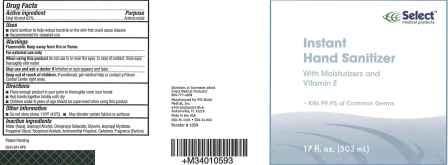 DRUG LABEL: ETHYL ALCOHOL
								
								
NDC: 68345-652 | Form: GEL
Manufacturer: PSS World Medical, Inc.
Category: otc | Type: HUMAN OTC DRUG LABEL
Date: 20100421

ACTIVE INGREDIENTS: ALCOHOL 0.62 mL/1 mL

PACKAGE LABEL

Select medical products Instant Hand Sanitizer

DIRECTIONS:
Place enough product in your palm to thoroughly cover your hands
Rub hands together briskly until dry
Children under 6 years of age should be supervised when using this product.

INACTIVE INGREDIENT

Inactive ingredients Water (Aqua), Isopropyl Alcohol, Diisopropyl Sebacate, Glycerin, Isopropyl Myristate, Propylene Glycol, Tocopheryl Acetate, Aminomethyl Propanol, Carbomer, Fragrance (Parfum)

Warnings
Flammable. Keep away from fire or flame.For external use only
When using this product do not use in or near the eyes. In case of contact, rinse eyes thoroughly with water.
Stop use and ask a doctor if irritation or rash appears and lasts
Keep out of reach of children. If swallowed, get medical help or contact a Poison Control Center right away

Active Ingredient Purpose
Ethyl Alcohol 62% Antimicrobial